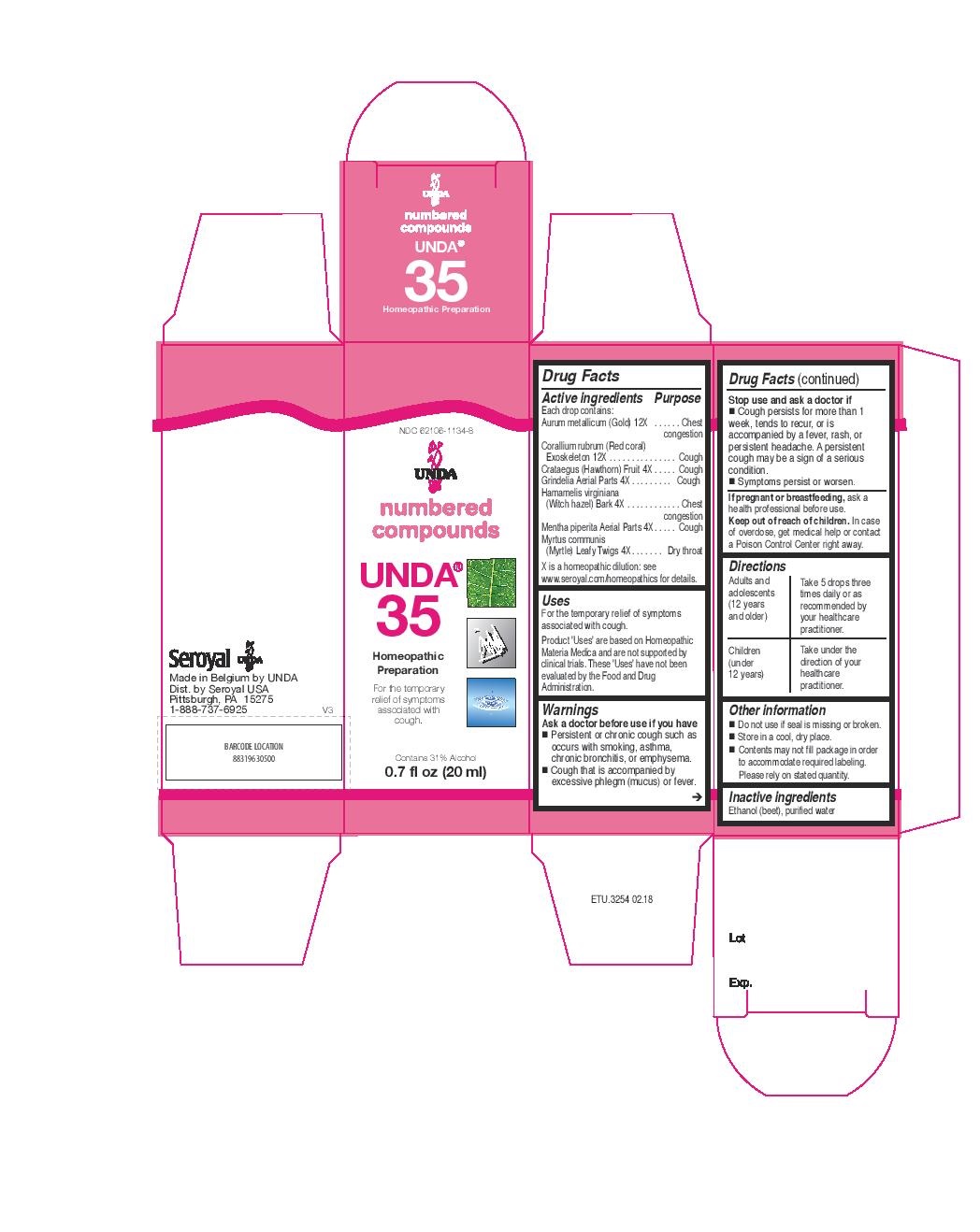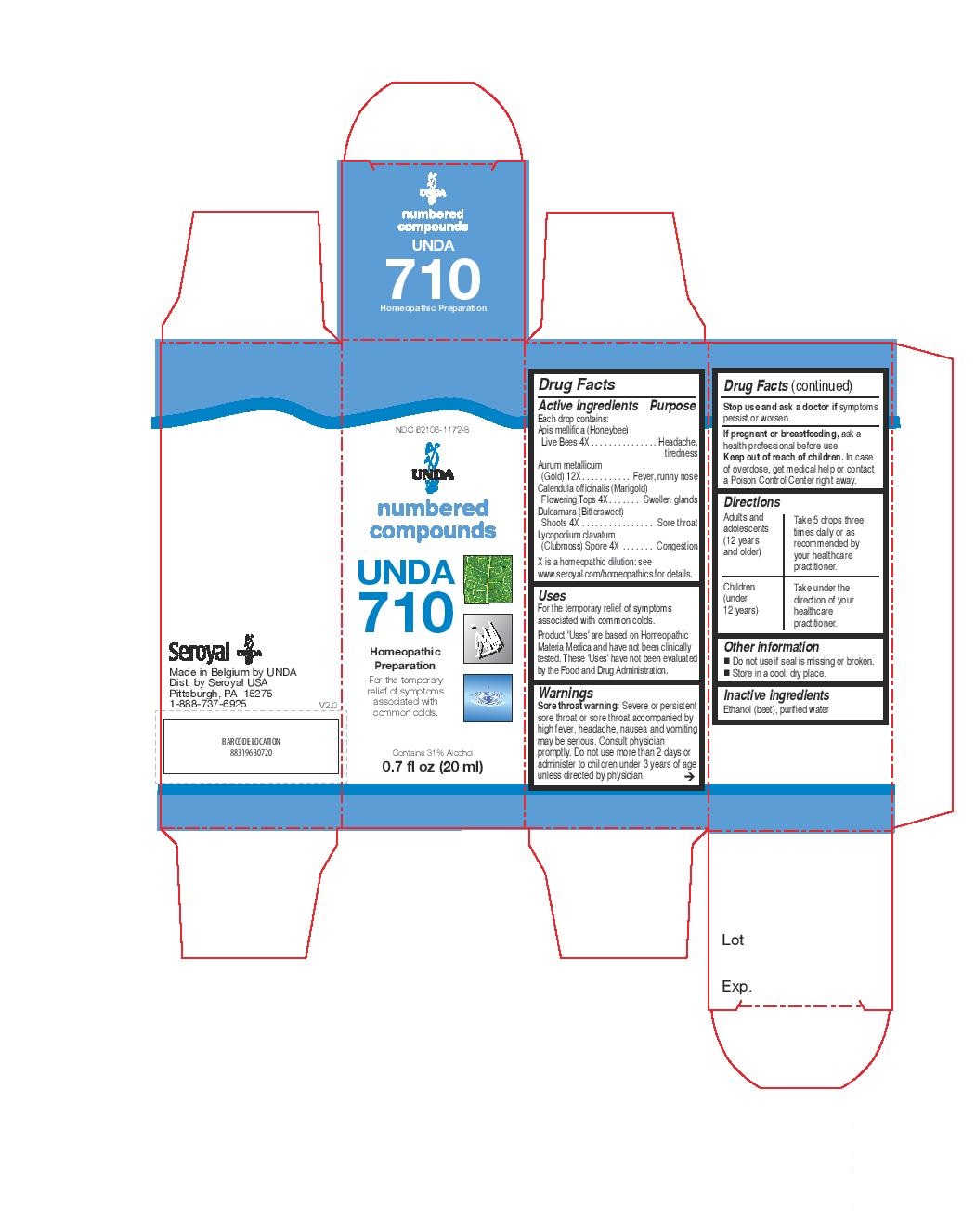 DRUG LABEL: UNDA 35
NDC: 62106-1134 | Form: LIQUID
Manufacturer: Seroyal USA
Category: homeopathic | Type: HUMAN OTC DRUG LABEL
Date: 20221109

ACTIVE INGREDIENTS: GOLD 12 [hp_X]/20 mL; CORALLIUM RUBRUM EXOSKELETON 12 [hp_X]/20 mL; CRATAEGUS FRUIT 4 [hp_X]/20 mL; GRINDELIA HIRSUTULA FLOWERING TOP 4 [hp_X]/20 mL; HAMAMELIS VIRGINIANA ROOT BARK/STEM BARK 4 [hp_X]/20 mL; MENTHA PIPERITA 4 [hp_X]/20 mL; MYRTUS COMMUNIS TOP 4 [hp_X]/20 mL
INACTIVE INGREDIENTS: ALCOHOL; WATER

UNDA 35 and UNDA 710

Active ingredients

Each drop contains:
Aurum metallicum (Gold) 12X
Corallium rubrum (Red coral) Exoskeleton 12X
Crataegus (Hawthorn) Fruit 4X
Grindelia Aerial Parts 4X
Hamamelis virginiana (Witch hazel) Bark 4X
Mentha piperita Aerial Parts 4X
Myrtus communis (Myrtle) Leafy Twigs 4X

Uses
For the temporary relief of symptoms associated with cough.

Warnings

Ask a doctor before use if you have
Persistent or chronic cough such as occurs with smoking, asthma, chronic bronchitis, or emphysema.
Cough that is accompanied by excessive phlegm (mucus) or fever.
Stop use and ask a doctor if
Cough persists for more than 1 week, tends to recur, or is accompanied by a fever, rash, or
persistent headache. A persistent cough may be a sign of a serious condition.
Symptoms persist or worsen.
If pregnant or breastfeeding, ask a health professional before use.
Keep out of reach of children. In case of overdose, get medical help or contact a Poison Control Center right away.

PREGNANCY OR BREAST FEEDING

If pregnant or breastfeeding, ask a health professional before use.

Keep out of reach of children.

Stop use and ask a doctor if
Cough persists for more than 1 week, tends to recur, or is accompanied by a fever, rash, or persistent headache. A persistent
cough may be a sign of a serious condition.
Symptoms persist or worsen.

OVERDOSAGE

In case of overdose, get medical help or contact a Poison Control Center right away.

Inactive ingredients
Ethanol (beet), purified water

Other information
Do not use if seal is missing or broken.
Store in a cool, dry place.
Contents may not fill package in order to accommodate required labeling. Please rely on stated quantity.

Directions

Adults and adolescents (12 years and older): Take 5 drops three times daily or as
recommended by your healthcare practitioner.

Children (under 12 years): Take under the direction of your
healthcare practitioner.

Uses
For the temporary relief of symptoms associated with cough.

Directions

Adults and adolescents (12 years and older): Take 5 drops three times daily or as
recommended by your healthcare practitioner.

Children (under 12 years): Take under the direction of your healthcare practitioner.

Active ingredients
Each drop contains:
Apis mellifica (Honeybee) Live Bees 4X
Aurum metallicum (Gold) 12X
Calendula officinalis (Marigold) Flowering Tops 4X
Dulcamara (Bittersweet) Shoots 4X
Lycopodium clavatum (Clubmoss) Spore 4X

Uses
For the temporary relief of symptoms associated with common colds.

Warning

Sore throat warning: Severe or persistent sore throat or sore throat accompanied

by high fever, headache, nausea and vomiting maybe serious.

Consult physician promptly.

Do not use more than 2 days or administer to children under 3 years of age unless directed by physician.

Stop use and ask a doctor if symptoms persist or worsen.
If pregnant or breastfeeding, ask a health professional before use.
Keep out of reach of children.

In case of overdose, get medical help or contact a Poison Control Center right away.

Do not use more than 2 days or administer to children under 3 years of age unless directed by physician.

Stop use and ask a doctor if symptoms persist or worsen.

PREGNANCY OR BREAST FEEDING

If pregnant or breastfeeding, ask a health professional before use.

Keep out of reach of children.

OVERDOSAGE

In case of overdose, get medical help or contact a Poison Control Center right away.

Inactive ingredients
Ethanol (beet), purified water

Directions

Adults and adolescents (12 years and older): Take 5 drops three
times daily or as recommended by your healthcare practitioner.

Children (under 12 years): Take under the direction of your
healthcare practitioner.

Uses
For the temporary relief of symptoms associated with common colds.

Directions

Adults and adolescents (12 years and older): Take 5 drops three
times daily or as recommended by your healthcare practitioner.

Children (under 12 years): Take under the direction of your
healthcare practitioner.

Other information
Do not use if seal is missing or broken.
Store in a cool, dry place.

PACKAGE LABEL

NDC 62106-1134-8

UNDA

numbered compounds

UNDA 35

Homeopathic Preparation

For the temporary relief of symptoms
associated with cough.

Contains 31% Alcohol
0.7 fl oz (20 mL)

PACKAGE LABEL

NDC 62106-1172-8

UNDA

numbered compounds

UNDA 710

Homeopathic Preparation

For the temporary relief of

symptoms associated with
common colds.

Contains 30% Alcohol
0.7 fl oz (20 ml)